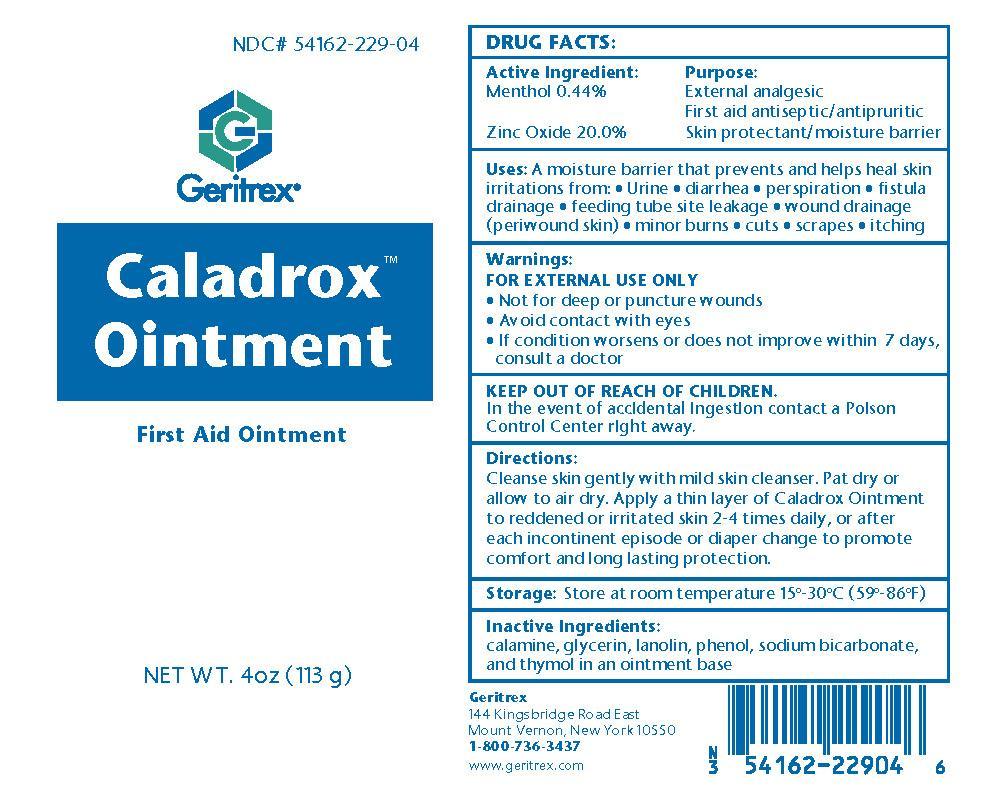 DRUG LABEL: Caladrox
NDC: 54162-229 | Form: OINTMENT
Manufacturer: Geritrex LLC
Category: otc | Type: HUMAN OTC DRUG LABEL
Date: 20150929

ACTIVE INGREDIENTS: MENTHOL 0.44 g/100 g; ZINC OXIDE 20 g/100 g
INACTIVE INGREDIENTS: GLYCERIN; LANOLIN; PHENOL; SODIUM BICARBONATE; THYMOL; SODIUM LAURETH SULFATE; METHYLPARABEN; PROPYLPARABEN; DMDM HYDANTOIN; STEARYL ALCOHOL; PROPYLENE GLYCOL; SORBITAN SESQUIOLEATE; MINERAL OIL; PETROLATUM; WATER

Caladrox Ointment

Drug Facts

Active Ingredient: Purpose:

Menthol 0.44% External analgesic

First aid antiseptic / antipruritic

Zinc Oxide 20.0% Skin protectant / moisture barrier

Uses

A moisture barrier that prevents and helps heal skin irritation from Urine, diarrhea, perspiration, fistula drainge, feeding tube site leakage, wound drainage (peri-wound skin), minor burns, cuts, scrapes, itching

Directions

Cleanse skin gently with mild skin cleanser. Pat dry or allow to air dry. Apply a thin layer of Caladrox Ointment to reddened or irritated skin 2-4 times daily or after each incontinent episode or diaper change to promote comfort and long lasting protection

Warnings

FOR EXTERNAL USE ONLY

Not for deep or puncture wounds

Avoid contact with eyes

If condition worsens or does not improve within 7 days, consult a doctor

Inactive Ingredients

Calamine, DMDM Hydantoin, Glycerin, Lanolin, Methylparaben, Mineral Oil, Petrolatum, Phenol, Propylparaben, Propylene Glycol, Purified Water, Sodium Laureth Sulfate, Stearyl Alcohol, Sorbitan Sesquioleate, Sodium bicarbonate and Thymol

KEEP OUT OF REACH OF CHILDREN

In the event of accidental ingestion contact a Poison Control Center right away

Storage

Store at room temperature 15°-30°C (59°-86°F)

DOSAGE AND ADMINISTRATION

Apply a thin layer of Caladrox Ointment to reddened or irritated skin 2-4 times daily.